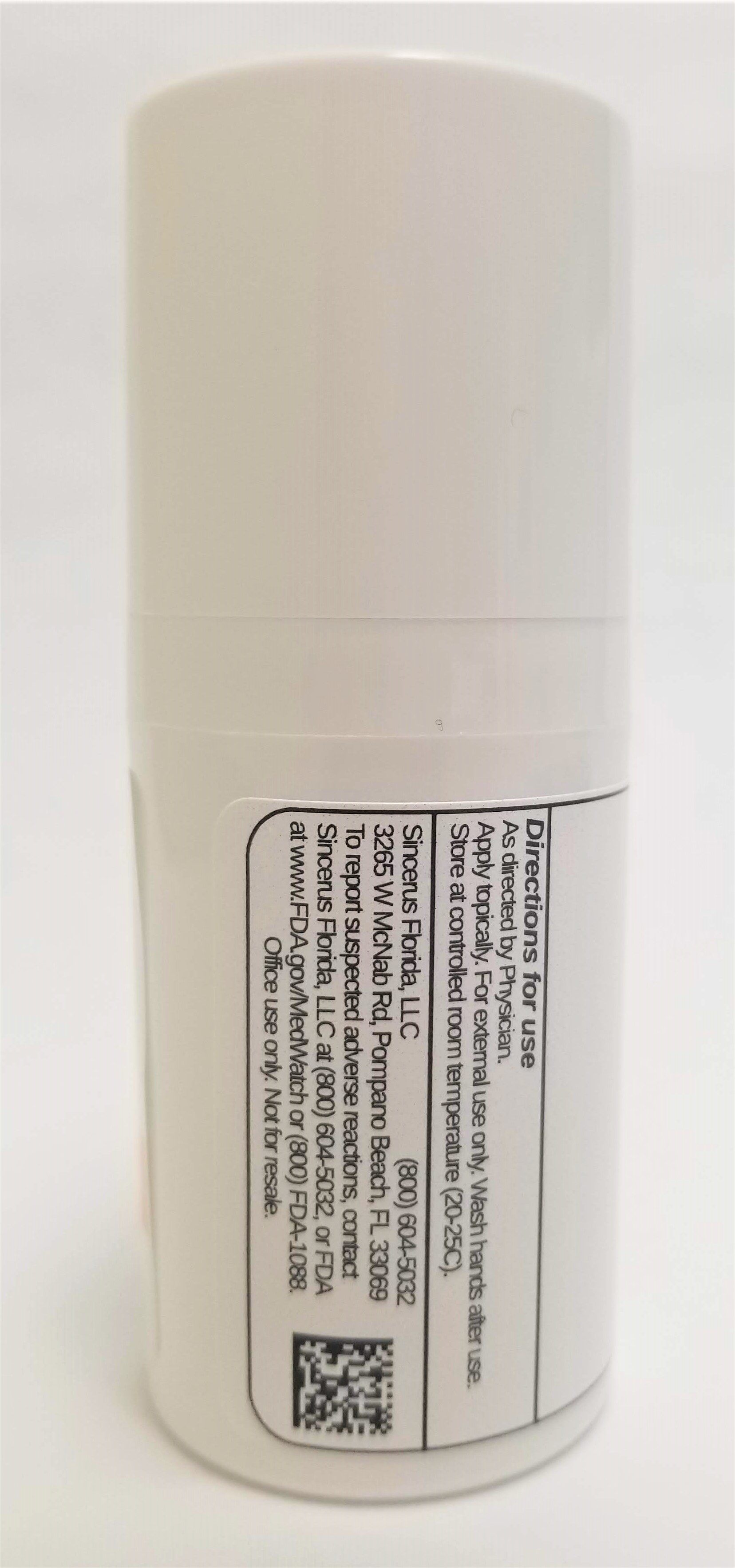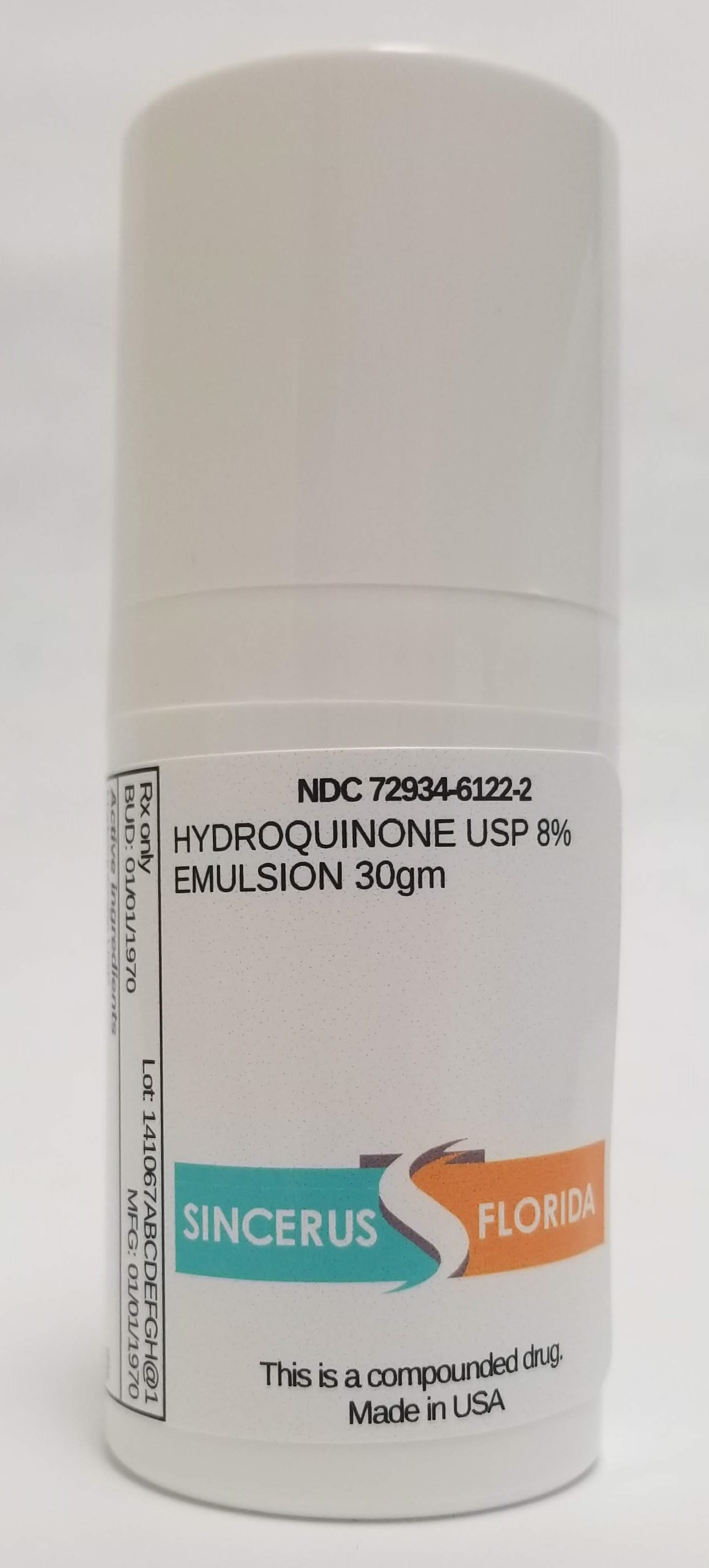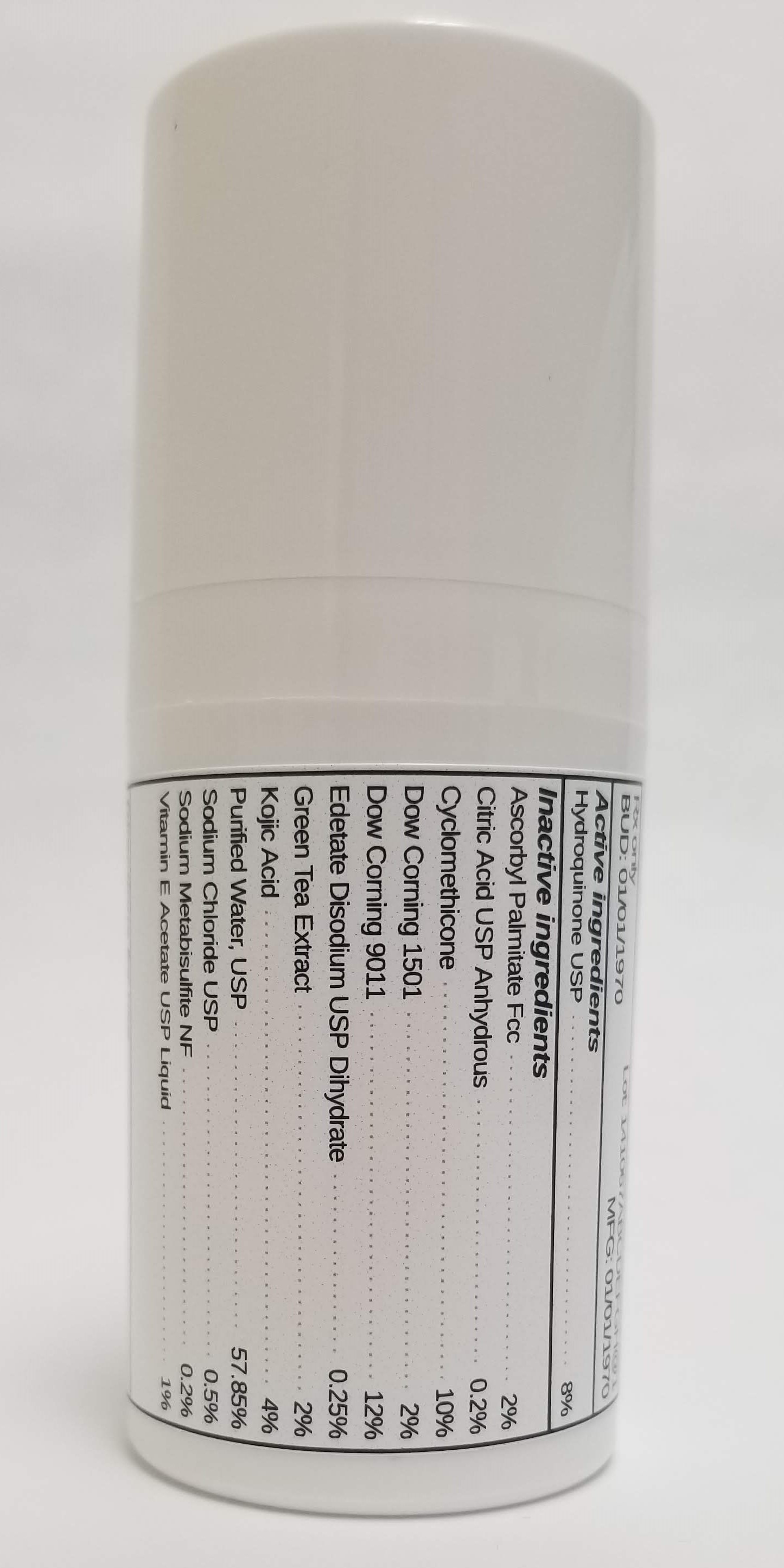 DRUG LABEL: HYDROQUINONE 8%.
NDC: 72934-6122 | Form: EMULSION
Manufacturer: Sincerus Florida, LLC
Category: prescription | Type: HUMAN PRESCRIPTION DRUG LABEL
Date: 20190520

ACTIVE INGREDIENTS: HYDROQUINONE 8 g/100 g

HYDROQUINONE 8%